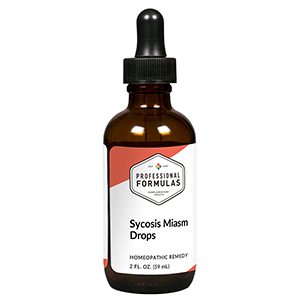 DRUG LABEL: Sycosis Miasm Drops
NDC: 63083-2062 | Form: LIQUID
Manufacturer: Professional Complementary Health Formulas
Category: homeopathic | Type: HUMAN OTC DRUG LABEL
Date: 20190815

ACTIVE INGREDIENTS: SILVER NITRATE 30 [hp_X]/59 mL; ARSENIC TRIOXIDE 30 [hp_X]/59 mL; LYCOPODIUM CLAVATUM SPORE 30 [hp_X]/59 mL; SODIUM SULFATE 30 [hp_X]/59 mL; NITRIC ACID 30 [hp_X]/59 mL; PULSATILLA MONTANA WHOLE 30 [hp_X]/59 mL; SMILAX ORNATA ROOT 30 [hp_X]/59 mL; THUJA OCCIDENTALIS LEAF 30 [hp_X]/59 mL; GONORRHEAL URETHRAL SECRETION HUMAN 30 [hp_X]/59 mL
INACTIVE INGREDIENTS: ALCOHOL; WATER

C62

ACTIVE INGREDIENTS

Argentum nitricum 30X
Arsenicum album 30X
Lycopodium clavatum 30X
Natrum sulphuricum 30X
Nitricum acidum 30X
Pulsatilla 30X
Sarsaparilla 30X
Thuja occidentalis 30X
Medorrhinum 30X, 60X, 100X

QUESTIONS

Professional Formulas

PO Box 2034 Lake Oswego, OR 97035

INDICATIONS

For the temporary relief of minor joint pain or inflammation, warts, urinary discomfort or difficulty, or forgetfulness consistent with classical sycosis miasm.*

PURPOSE

*Claims based on traditional homeopathic practice, not accepted medical evidence. Not FDA evaluated.

WARNINGS

In case of overdose, get medical help or contact a poison control center right away.

Keep out of the reach of children.

PREGNANCY OR BREAST FEEDING

If pregnant or breastfeeding, ask a healthcare professional before use.

DIRECTIONS

Place drops under tongue 30 minutes before/after meals. Adults and children 12 years and over: Take 10 drops up to 3 times per day. Consult a physician for use in children under 12 years of age.

OTHER INFORMATION

Tamper resistant. If seal is broken, do not use. After opening, close container tightly and store at room temperature away from heat.

INACTIVE INGREDIENTS

20% ethanol, purified water.

LABEL

Est 1985

Professional Formulas

Complementary Health

Sycosis Miasm Drops

Homeopathic Remedy

2 FL. OZ. (59 mL)